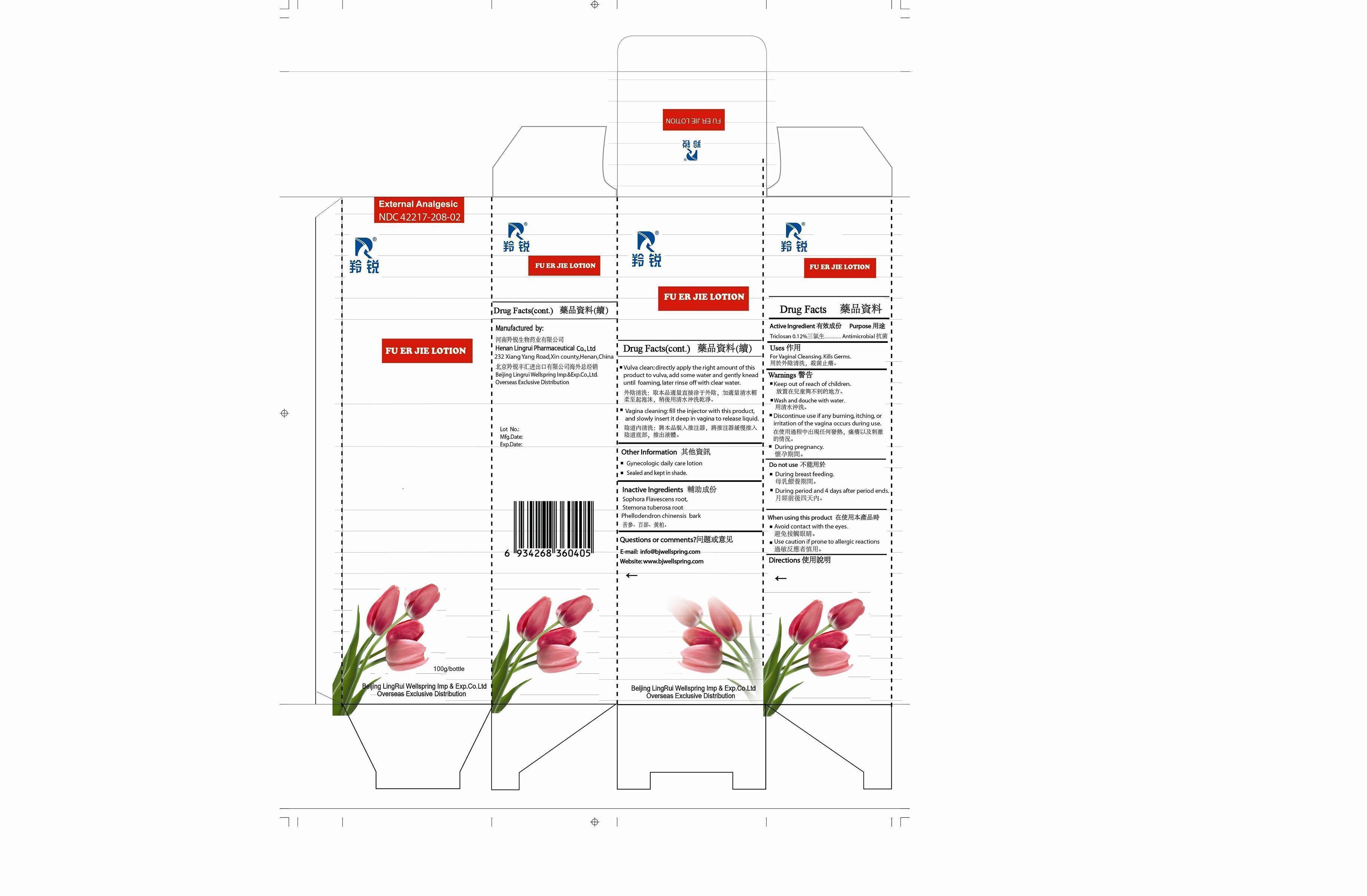 DRUG LABEL: Fu Er Jie
NDC: 42217-208 | Form: LOTION
Manufacturer: Henan Lingrui Pharmaceutical Co Ltd
Category: otc | Type: HUMAN OTC DRUG LABEL
Date: 20150319

ACTIVE INGREDIENTS: TRICLOSAN 0.12 g/100 g
INACTIVE INGREDIENTS: SOPHORA FLAVESCENS ROOT; STEMONA TUBEROSA ROOT; PHELLODENDRON CHINENSIS BARK

Henan Lingrui Pharmaceutical Co Ltd

Active Ingredient

Triclosan 0.12%

Purpose

Antimicrobial

Uses

For Vaginal Cleansing. Kills Germs.

Warning

Keep out of reach of children.

Wash and douche with water.

WARNINGS

Discontinue use if any burning, itching, or irritation of the vagina occurs during use.

During pregnancy.

Do not use during breast feeding.

Do not use during period and 4 days after period ends.

When using this product

Avoid contact with the eyes.

Use caution if prone to allergic reactions.

Directions

Vulva clean: directly apply the right amount of this product to vulva, add some water and gently knead until foaming, later rinse off with clear water.

Vagina cleaning: fill the injector with this product, and slowly insert it deep in vagina to release liquid.

Other Information

Gynecologic daily care lotion

Sealed and kept in shade.

Inactive Ingredients

SOPHORA FLAVESCENS ROOT, STEMONA TUBEROSA ROOT, PHELLODENDRON CHINENSIS BARK

Questions or Comments?

E-mail: info@bjwellspring.com

Manufactured by

Henan Lingrui Pharmaceutical Co.; Ltd.

232 Xiang Yang Road, Xin County, Henan, China

Beijing Lingrui Wellspring Imp. & Exp. Co.; Ltd.

Overseas Exclusive Distribution